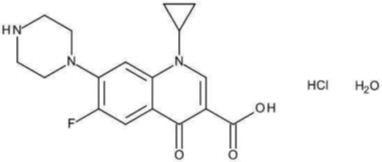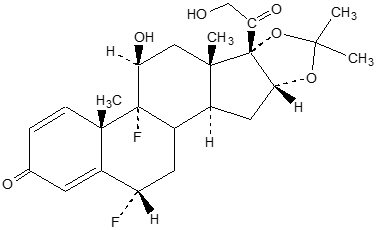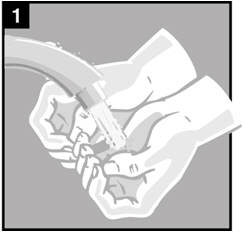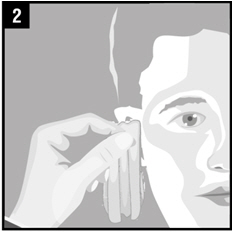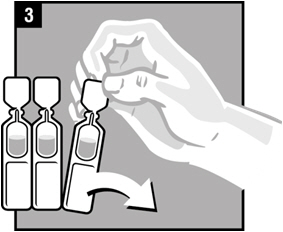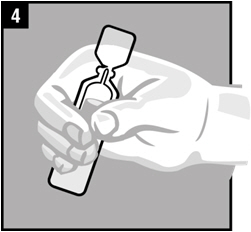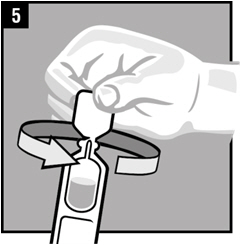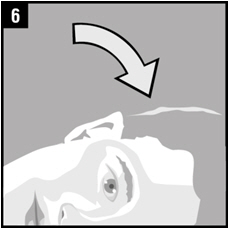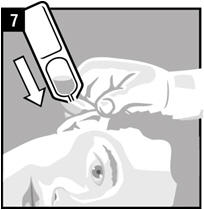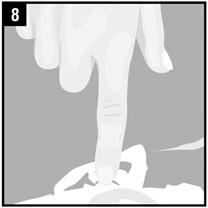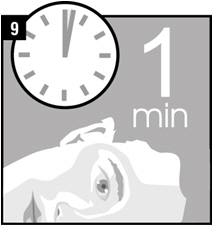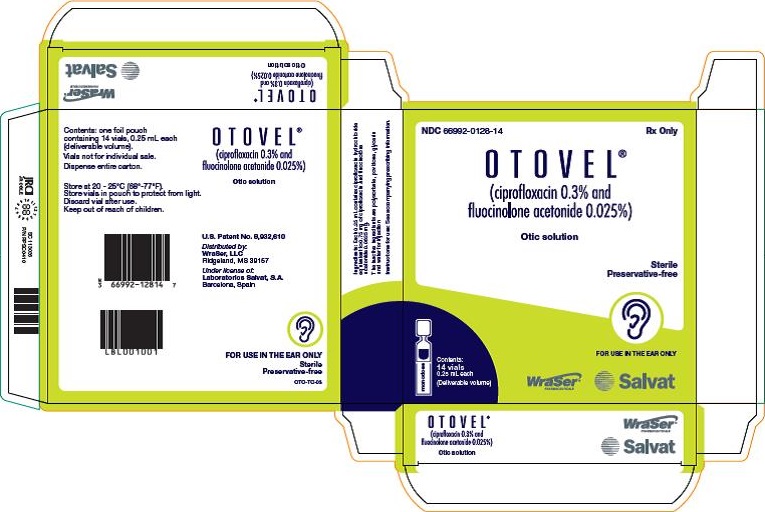 DRUG LABEL: OTOVEL
NDC: 66992-128 | Form: SOLUTION
Manufacturer: WraSer LLC
Category: prescription | Type: HUMAN PRESCRIPTION DRUG LABEL
Date: 20241009

ACTIVE INGREDIENTS: CIPROFLOXACIN 0.75 mg/0.25 mL; FLUOCINOLONE ACETONIDE 0.0625 mg/0.25 mL
INACTIVE INGREDIENTS: GLYCERIN; POLYSORBATE 80; POVIDONE K90; WATER

HIGHLIGHTS OF PRESCRIBING INFORMATION

These highlights do not include all the information needed to use OTOVEL safely and effectively. See full prescribing information for OTOVEL.
OTOVEL (ciprofloxacin and fluocinolone acetonide) otic solution
Initial U.S. Approval: 2016

1 INDICATIONS AND USAGE

OTOVEL is a combination of ciprofloxacin, a fluoroquinolone antibacterial, and fluocinolone acetonide, a corticosteroid, indicated for the treatment of acute otitis media with tympanostomy tubes (AOMT) in pediatric patients (aged 6 months and older) due to Staphylococcus aureus, Streptococcus pneumoniae, Haemophilus influenzae, Moraxella catarrhalis, and Pseudomonas aeruginosa (1)

2 DOSAGE AND ADMINISTRATION

- OTOVEL is for otic administration only. It is not for ophthalmic use, or for injection. (2)
- Instill the contents of one single-dose vial (0.25 mL) into the affected ear canal twice daily for 7 days. (2)
- Use this dosing regimen for patients aged 6 months and older. (2)

3 DOSAGE FORMS AND STRENGTHS

Otic Solution: Each single-dose vial of OTOVEL (ciprofloxacin 0.3 % and fluocinolone acetonide 0.025 %) delivers 0.25 mL of solution equivalent to ciprofloxacin 0.75 mg and fluocinolone acetonide 0.0625 mg.

4 CONTRAINDICATIONS

OTOVEL is contraindicated in:

- Patients with known hypersensitivity to fluocinolone acetonide or other corticosteroids, ciprofloxacin or other quinolones, or to any component of OTOVEL. (4)
- Viral infections of the external ear canal, including varicella and herpes simplex infections and fungal otic infections. (4)

5 WARNINGS AND PRECAUTIONS

- Hypersensitivity: Discontinue use at the first appearance of a skin rash or any other sign of hypersensitivity. (5.1)
- Potential for Microbial Overgrowth:Prolonged use may result in the overgrowth of non-susceptible bacteria and fungi. If such infections occur, discontinue use and institute alternative therapy. (5.2)

6 ADVERSE REACTIONS

The most common adverse reactions that occurred in ≥1 patient were otorrhea, excessive granulation tissue, ear infection, ear pruritus, tympanic membrane disorder, auricular swelling and balance disorder (6.1)

To report SUSPECTED ADVERSE REACTIONS, contact WraSer, LLC at 1-888-252-3901 or FDA at 1-800-FDA-1088 or www.fda.gov/medwatch.

FULL PRESCRIBING INFORMATION

1 INDICATIONS AND USAGE

OTOVEL is indicated for the treatment of acute otitis media with tympanostomy tubes (AOMT) in pediatric patients (aged 6 months and older) due to Staphylococcus aureus, Streptococcus pneumoniae, Haemophilus influenzae, Moraxella catarrhalis, and Pseudomonas aeruginosa.

2 DOSAGE AND ADMINISTRATION

- OTOVEL is for otic use only. It is not for ophthalmic use, or for injection.

The recommended dosage regimen is as follows:

- Instill the contents of one single-dose vial 0.25 mL into the affected ear canal twice daily (approximately every 12 hours) for 7 days. Use this dosing for patients aged 6 months of age and older.
- Warm the solution by holding the vial in the hand for 1 to 2 minutes. This is to avoid dizziness, which may result from the instillation of a cold solution into the ear canal.
- The patient should lie with the affected ear upward, and then instill the medication.
- Pump the tragus 4 times by pushing inward to facilitate penetration of the medication into the middle ear.
- Maintain this position for 1 minute. Repeat, if necessary, for the opposite ear [see Instructions for Use] .

3 DOSAGE FORMS AND STRENGTHS

Otic Solution: Each single-dose vial of OTOVEL (ciprofloxacin 0.3 % and fluocinolone acetonide 0.025 %) delivers 0.25 mL of solution equivalent to ciprofloxacin 0.75 mg and fluocinolone acetonide 0.0625 mg.

4 CONTRAINDICATIONS

OTOVEL is contraindicated in:

- Patients with known hypersensitivity to fluocinolone acetonide or other corticosteroids, ciprofloxacin or other quinolones, or to any other components of OTOVEL.
- Viral infections of the external ear canal, including varicella and herpes simplex infections and fungal otic infections.

5 WARNINGS AND PRECAUTIONS

5.1 Hypersensitivity Reactions

OTOVEL should be discontinued at the first appearance of a skin rash or any other sign of hypersensitivity. Serious and occasionally fatal hypersensitivity (anaphylactic) reactions, some following the first dose, have been reported in patients receiving systemic quinolones. Some reactions were accompanied by cardiovascular collapse, loss of consciousness, angioedema (including laryngeal, pharyngeal or facial edema), airway obstruction, dyspnea, urticaria and itching. Serious acute hypersensitivity reactions may require immediate emergency treatment.

5.2 Potential for Microbial Overgrowth with Prolonged Use

Prolonged use of OTOVEL may result in overgrowth of non-susceptible bacteria and fungi. If the infection is not improved after one week of treatment, cultures should be obtained to guide further treatment. If such infections occur, discontinue use and institute alternative therapy.

5.3 Continued or Recurrent Otorrhea

If otorrhea persists after a full course of therapy, or if two or more episodes of otorrhea occur within 6 months, further evaluation is recommended to exclude an underlying condition such as cholesteatoma, foreign body, or a tumor.

6 ADVERSE REACTIONS

The following serious adverse reactions are described elsewhere in the labeling:

Hypersensitivity Reactions [ see Warnings and Precautions (5.1)]

6.1 Clinical Trials Experience

Because clinical trials are conducted under widely varying conditions, adverse reaction rates observed in the clinical trials of a drug cannot be directly compared to rates in the clinical trials of another drug and may not reflect the rates observed in practice.

In clinical trials, 224 patients with AOMT were treated with OTOVEL for a median duration of 7 days. All the patients received at least one dose of OTOVEL. There were 220 patients who received at least one dose of ciprofloxacin (CIPRO) and 213 patients received at least one dose of fluocinolone acetonide (FLUO).

The most common adverse reactions that occurred in 1 or more patients are as follows:

Table 1: Selected Adverse Reactions that Occurred in 1 or more Patients in the OTOVEL Group
Adverse Reactions [Selected adverse reactions that occurred in ≥ 1 patient in the OTOVEL group derived from all reported adverse events that could be related to the study drug or the drug class.] | Number (%) of Patients
Adverse Reactions [Selected adverse reactions that occurred in ≥ 1 patient in the OTOVEL group derived from all reported adverse events that could be related to the study drug or the drug class.] | OTOVEL N=224 | CIPRO N=220 | FLUO N=213
Otorrhea | 12 (5.4%) | 9 (4.1%) | 12 (5.6%)
Excessive granulation tissue | 3 (1.3%) | 0 (0.0%) | 2 (0.9%)
Ear infection | 2 (0.9%) | 3 (1.4%) | 1 (0.5%)
Ear pruritus | 2 (0.9%) | 1 (0.5%) | 1 (0.5%)
Tympanic membrane disorder | 2 (0.9%) | 0 (0.0%) | 0 (0.0%)
Auricular swelling | 1 (0.4%) | 1 (0.5%) | 0 (0.0%)
Balance disorder | 1 (0.4%) | 0 (0.0%) | 0 (0.0%)

6.2 Postmarketing Experience

The following adverse reactions have been identified during postapproval use of ciprofloxacin and fluocinolone acetonide otic solution, 0.3% / 0.025% outside the US. Because these reactions are reported voluntarily from a population of uncertain size, it is not always possible to reliably estimate their frequency or establish a causal relationship to drug exposure.

- Immune system disorders:allergic reaction.
- Infections and infestations:candidiasis.
- Nervous system disorders:dysgeusia, paresthesia (tingling in ears), dizziness, headache.
- Ear and labyrinth disorders:ear discomfort, hypoacusis, tinnitus, ear congestion.
- Vascular disorders:flushing.
- Skin and subcutaneous tissue disorders:skin exfoliation.
- Injury, poisoning and procedural complications:device occlusion (tympanostomy tube obstruction).

8 USE IN SPECIFIC POPULATIONS

8.1 Pregnancy

Risk Summary

OTOVEL is negligibly absorbed following otic administration and maternal use is not expected to result in fetal exposure to ciprofloxacin and fluocinolone acetonide [see Clinical Pharmacology (12.3)].

8.2 Lactation

Risk Summary

OTOVEL is negligibly absorbed by the mother following otic administration and breastfeeding is not expected to result in exposure of the infant to ciprofloxacin and fluocinolone acetonide [ see Clinical Pharmacology (12.3)].

8.4 Pediatric Use

OTOVEL has been studied in patients as young as 6 months in adequate and well-controlled clinical trials. No major differences in safety and effectiveness have been observed between adult and pediatric patients [ see Indications and Usage (1)and Dosage and Administration (2)].

8.5 Geriatric Use

Clinical studies of OTOVEL did not include sufficient numbers of subjects aged 65 years and over to determine whether they respond differently from younger subjects. Other reported clinical experience has not identified differences in responses between the elderly and younger patients.

10 OVERDOSAGE

Due to the characteristics of this preparation, no toxic effects are to be expected with an otic overdose of OTOVEL.

11 DESCRIPTION

OTOVEL (ciprofloxacin and fluocinolone acetonide) otic solution, 0.3% / 0.025% is a sterile, preservative-free, clear otic solution containing the fluoroquinolone antibacterial, ciprofloxacin hydrochloride, combined with the corticosteroid, fluocinolone acetonide. Each single-dose vial contains a deliverable volume of 0.25 mL solution of ciprofloxacin hydrochloride equivalent to 0.75 mg ciprofloxacin and 0.0625 mg fluocinolone acetonide. The pH of the solution ranges from 3.5 to 5.0. The inactive ingredients are polysorbate 80, glycerin, povidone K90F and water for injection.

Ciprofloxacin is available as the monohydrochloride, monohydrate salt of 1-cyclopropyl-6-fluoro-1,4-dihydro-4-oxo-7-(1-piperazinyl)-3-quinolinecarboxylic acid. Its molecular formula is C17H18FN3O3∙HCl∙H2O.

The chemical structure of ciprofloxacin hydrochloride is:

The chemical name of fluocinolone acetonide is (6α,11β,16α)-6,9-difluoro-11,21-dihydroxy- 16,17[(1-methylethylidene)bis(oxy)]-pregna-1,4-diene-3,20-dione, cyclic 16,17 acetal with acetone[67-73-2]. Its molecular formula is C24H30F2O6.

The chemical structure of fluocinolone acetonide is:

12 CLINICAL PHARMACOLOGY

12.1 Mechanism of Action

Ciprofloxacin is a fluoroquinolone antibacterial [ see Microbiology (12.4)].

Fluocinolone acetonide, a corticosteroid, inhibits the local biosynthesis of prostaglandins, which explains part of its anti-inflammatory efficacy. At the cellular level, corticosteroids induce peptides called lipocortins. Lipocortins antagonize phospholipase A2, an enzyme which causes the breakdown of leukocyte lysosomal membranes to release arachidonic acid. This action decreases the subsequent formation and release of endogenous inflammatory mediators including prostaglandins, kinins, histamine, liposomal enzymes and the complement system.

12.3 Pharmacokinetics

In two studies in children with AOMT aged ≥ 6 months to 12 years, blood samples were taken in subgroups of 16 and 14 patients, at Visit 1 (prior to the first dose) and Visit 3 (within 1 and 2 hours after the last dose) respectively, to determine the plasma concentrations of ciprofloxacin and/or fluocinolone acetonide following administration of OTOVEL otic solution at the recommended dosage regimen of 0.25 mL twice daily. Pharmacokinetic (PK) analysis resulted in only 1 sample showing a detectable concentration of ciprofloxacin in plasma of 3.0 mcg/L after 7 days of treatment, and no detectable concentrations in plasma of fluocinolone acetonide were observed. However, the sample with detectable ciprofloxacin concentrations was from a patient who had bilateral AOMT (protocol deviation because all patients participating in the PK study were to have unilateral otorrhea) and who received treatment in both ears with ciprofloxacin 0.3% otic solution, the active comparator.

12.4 Microbiology

Mechanism of Action

The bactericidal action of ciprofloxacin results from interference with the enzyme DNA gyrase, which is needed for the synthesis of bacterial DNA.

Resistance

Bacterial resistance to quinolones can develop through chromosomal or plasmid-mediated mechanisms.

In vitrostudies demonstrated cross-resistance between ciprofloxacin and some fluoroquinolones. There is generally no cross-resistance between ciprofloxacin and other classes of antibacterial agents such as beta-lactams or aminoglycosides.

Antimicrobial Activity

Ciprofloxacin has been shown to be active against most isolates of the following bacteria, both in vitroand clinically in otic infections [ see Indications and Usage (1)]:

Aerobic Bacteria:

Gram-positive Bacteria:
Staphylococcus aureus
Streptococcus pneumoniae

Gram-negative Bacteria:
Pseudomonas aeruginosa
Haemophilus influenzae
Moraxella catarrhalis

13 NONCLINICAL TOXICOLOGY

13.1 Carcinogenesis, Mutagenesis, Impairment of Fertility

Carcinogenesis

No long term studies of OTOVEL have been performed to evaluate carcinogenic potential.

Long-term carcinogenicity studies in mice and rats have been completed for ciprofloxacin. After daily oral doses of 750 mg/kg (mice) and 250 mg/kg (rats) were administered for up to 2 years, there was no evidence that ciprofloxacin had any carcinogenic or tumorigenic effects in these species.

Long-term animal studies have not been performed to evaluate the carcinogenic potential of fluocinolone acetonide.

Mutagenesis

Eight in vitromutagenicity tests have been conducted with ciprofloxacin, and the test results are listed below:

- Salmonella/Microsome Test (Negative)
- E. coliDNA Repair Assay (Negative)
- Mouse Lymphoma Cell Forward Mutation Assay (Positive)
- Chinese Hamster V79 Cell HGPRT Test (Negative)
- Syrian Hamster Embryo Cell Transformation Assay (Negative)
- Saccharomyces cerevisiaePoint Mutation Assay (Negative)
- Saccharomyces cerevisiaeMitotic Crossover and Gene Conversion Assay (Negative)
- Rat Hepatocyte DNA Repair Assay (Positive)

Thus, 2 of the 8 tests were positive, but results of the following 3 in vivotest systems gave negative results:

- Rat Hepatocyte DNA Repair Assay
- Micronucleus Test (Mice)
- Dominant Lethal Test (Mice)

Studies have not been performed to evaluate the mutagenic potential of fluocinolone acetonide. Some corticosteroids have been found to be genotoxic.

Impairment of Fertility

No reproduction toxicity studies were conducted with OTOVEL. Absorption of ciprofloxacin and fluocinolone acetonide following otic administration of OTOVEL at the recommended dosage is negligible [ see Clinical Pharmacology (12.3)].

14 CLINICAL STUDIES

Two phase 3 multicenter, randomized, double-blind, active-controlled, parallel group trials were conducted in 662 pediatric patients in total (aged 6 months to 12 years old) with AOMT, to assess the efficacy and safety of OTOVEL compared to ciprofloxacin otic solution and to fluocinolone acetonide otic solution (Trial 1 and Trial 2).

In both trials, the OTOVEL treatment arms showed significantly shorter times to cessation of otorrhea in comparison to both the ciprofloxacin and fluocinolone acetonide alone arms demonstrating the contribution of both components of OTOVEL. The results are presented in the table below:

Table 2: Results of the Primary Endpoint: Time to Cessation of Otorrhea (Trial 1 and Trial 2)
 | Treatment arm
Trial 1 | OTOVEL (N=112) | CIPRO (N=109) | FLUO (N=110)
Number (%) with cessation of otorrhea by Day 22 | 88 (78.6%) | 73 (67.0%) | 53 (48.2%)
Median time to cessation [Kaplan-Meier median estimate censored all subjects who did not have a cessation of otorrhea at the maximum time point of 22 days.] (days) | 3.75 | 7.69 | n.e.
p-value vs OTOVEL [Log-rank test stratified by age (patients younger than 3 years versus 3 years and older)] |  | <0.001 | <0.001
Trial 2 | OTOVEL (N=111) | CIPRO (N=112) | FLUO (N=108)
Number (%) with cessation of otorrhea by Day 22 | 87 (78.4%) | 77 (68.8%) | 47 (43.5%)
Median time to cessation (days) | 4.94 | 6.83 | n.e.
p-value vs OTOVEL |  | 0.028 | <0.001
n.e.: not estimable because the number of censored patients was greater than the number of patients with cessation of otorrhea

16 HOW SUPPLIED/STORAGE AND HANDLING

How supplied

OTOVEL (ciprofloxacin and fluocinolone acetonide) otic solution, 0.3 %/0.025 %, is a sterile, preservative-free, clear otic solution supplied in blue translucent single-dose 0.25 mL vials. Fourteen single-dose vials are packaged in a protective foil pouch contained in a carton (NDC 66992-128-14).

Storage

Store at 20°-25°C (68°-77°F); excursions permitted to 15°-30°C (59°-86°F) [see USP Controlled Room Temperature]. Protect from light; store unused vials in pouch and discard 7 days after opening the pouch. Do not open until ready to use. Discard vial after use.

17 PATIENT COUNSELING INFORMATION

Advise the patient or caregiver to read the FDA-approved patient labeling (Patient Informationand Instructions for Use).

Administration Instructions

- Advise patients that OTOVEL is for otic use only. It is not to be used in the eyes.
- Advise patients to warm the otic solution by holding the vial in the hand for 1 to 2 minutes before instilling it in the ear, to avoid dizziness.

Hypersensitivity Reactions

- Advise patients to immediately discontinue OTOVEL at the first appearance of a skin rash or any other sign of hypersensitivity [see Warnings and Precautions (5.1)]

OTOVEL is:

Distributed by:
WraSer, LLC
Ridgeland, MS 39157

Under license of Laboratorios SALVAT, S.A.

OTOVEL is a registered trademark of Laboratorios Salvat, S.A.

U.S. Patent No: 8,932,610

OTO-PIAG-01

PATIENT INFORMATION
OTOVEL (OH-toe-vel)
(ciprofloxacin and fluocinolone acetonide)
otic Solution

What is OTOVEL?

OTOVEL is a prescription medicine used in the ear only (otic use) that contains 2 medicines, a quinolone antibiotic medicine called ciprofloxacin and a corticosteroid medicine called fluocinolone acetonide. OTOVEL is used in children 6 months of age and older to treat a type of middle ear infection called acute otitis media with tympanostomy tubes (AOMT) in children who have a tube in their eardrum known as a tympanostomy tube, to prevent having too much fluid in the middle ear.

It is not known if OTOVEL is safe and effective in children under 6 months of age.

Who should not use OTOVEL?

Do not use OTOVEL if you:

- Are allergic to ciprofloxacin, quinolones, fluocinolone acetonide, corticosteroids or any of the ingredients in OTOVEL. See the end of this Patient Information leaflet for a complete list of ingredients in OTOVEL.
- Have an outer ear canal infection caused by certain viruses including chicken pox (varicella) and the herpes simplex virus.
- Have an ear infection caused by a fungus.

What should I tell my healthcare provider before using OTOVEL?

Before using OTOVEL, tell your healthcare provider about all of your medical conditions, including if you:

- Are pregnant or plan to become pregnant, although OTOVEL is not expected to harm your baby.
- Are breastfeeding or plan to breastfeed, although OTOVEL is not expected to pass into your breast milk and to harm your baby.

Tell your healthcare provider about all the medicines you take,including prescription and over-the-counter medicines, vitamins, and herbal supplements. Know the medicines you take. Keep a list of them to show your healthcare provider and pharmacist when you get a new medicine.

How should I use OTOVEL?

- Read the detailed Instructions for Use that come with OTOVEL.
- Use OTOVEL exactly as your healthcare provider tells you to use it.
- OTOVEL is for use in the ear only(otic use). Do not inject OTOVEL or use OTOVEL in the eye.
- OTOVEL comes as a liquid in single-dose vials.
- Apply the entire dose of OTOVEL from 1 of the single-dose vials, into the affected ear 2 times a day (for a total of 2 single-dose vials a day) for 7 days. Each dose should be about 12 hours apart.

If your symptoms do not improve after 7 days of treatment with OTOVEL, call your healthcare provider.

- Call your healthcare provider right away if:
  - have fluid that continues to drain from your ear (otorrhea) after you have finished your treatment with OTOVEL.
  - you have fluid that drains from your ear 2 or more times within 6 months after you stop treatment with OTOVEL.

What are the possible side effects of OTOVEL?

OTOVEL may cause serious side effects, including:

- Allergic reactions.Stop using OTOVEL and call your health care provider if you have any of the following signs or symptoms of an allergic reaction:
  - hives (urticaria)
  - swelling of your face, lips, mouth, or tongue.
  - rash
  - itching
  - trouble breathing
  - dizziness, fast heartbeat, or pounding in your chest

The most common side effects that occurred during the testing of OTOVEL include:

-
  - fluid that continues to drain from your ear (otorrhea)
  - extra tissue that grows on a part of the ear that has been injured (excessive granulation tissue)
  - ear pain
  - ear infection
  - ear itching (pruritus)
  - swelling of the outer or inside part of the ear
  - balance problems

If an allergic reaction to OTOVEL occurs, stop using the product and contact your doctor.

Tell your healthcare provider if you have any side effect that bothers you or that does not go away.

These are not all the possible side effects of OTOVEL. For more information, ask your healthcare provider or pharmacist. Call your doctor for medical advice about side effects. You may report side effects to FDA at 1-800-FDA-1088.

How should I store OTOVEL?

- Store unopened OTOVEL vials in the protective foil pouch they come in.
- Store OTOVEL at 20°-25°C (68°-77°F).
- Keep OTOVEL out of light.
- Do not open the OTOVEL foil pouch until ready to use.
- When the OTOVEL foil pouch is opened, use the vials within 7 days.
- When a OTOVEL vial is opened, use it right away.

Keep OTOVEL and all medicines out of the reach of children.

General information about the safe and effective use of OTOVEL.

Medicines are sometimes prescribed for purposes other than those listed in a Patient Information leaflet. Do not use OTOVEL for a condition for which it was not prescribed. Do not give OTOVEL to other people, even if they have the same symptoms that you have. It may harm them.

This Patient Information leaflet summarizes the most important information about OTOVEL. If you would like more information, talk with your healthcare provider. You can ask your pharmacist or healthcare provider for information about OTOVEL that is written for healthcare professionals.

What are the ingredients in OTOVEL?

Active ingredients:ciprofloxacin and fluocinolone acetonide.

Inactive ingredients:polysorbate, povidone, glycerin, and water.

Distributed by:WraSer, LLC, Ridgeland, MS 39157.

Under license of Laboratorios Salvat, S.A.

For more information, go to www.wraser.comor call 1-888-252-3901.

This Patient Information has been approved by the U.S. Food and Drug Administration

Issued: 06/2021

INSTRUCTIONS FOR USE OTOVEL (OH-toe-vel) (ciprofloxacin and fluocinolone acetonide) otic solution

Read this Instructions for Use that comes with OTOVEL before you start using it and each time you get a refill. There may be new information. This information does not take the place of talking with your healthcare provider about your medical condition or treatment.

Important information about OTOVEL:

- OTOVEL is for use in the ear only (otic use). Do not inject OTOVEL or use OTOVEL in the eye.
- Use OTOVEL Solution exactly as your healthcare provider tells you to use it.

How should I use OTOVEL?

Step 1. | You or your caregiver should wash their hands with soap and water.
Step 2. | Gently clean any fluid (discharge) from the outer ear using a clean cloth or tissue. Do notput a cotton swab or any other object in the ear canal.
Step 3. | Remove OTOVEL from the protective foil pouch. Pull apart 1 single-dose vial of OTOVEL as shown, by tearing along the dotted lines (perforations) until it is fully separated.
Step 4. | Warm the dose of OTOVEL by holding the vial in your hand for 1 to 2 minutes.
Step 5. | Twist off the vial cap in the direction of the arrow as shown.
Step 6. | The person receiving OTOVEL should be on his/her side with the infected ear up as shown.
Step 7. | Hold the vial of OTOVEL in your hand and place the vial close to the ear. Let the entire dose of OTOVEL fall into the affected ear.
Step 8. | Gently press the part of the ear known as the tragus 4 timesusing a pumping motion as shown. This will allow the drops of OTOVEL to enter the middle ear.
Step 9. | Remain on your side with the affected ear facing upward for 1 minute.
Step 10. | If your healthcare provider has told you to use OTOVEL in both ears, repeat Steps 2-9 for the other ear.
Step 11. | Safely throw away OTOVEL vials after use.

This Instructions for Use has been approved by the Food and Drug Administration.

PRINCIPAL DISPLAY PANEL - 0.25 mL Vial Pouch Carton

NDC 66992-128-14
Rx Only

Ciprofloxacin 0.3% and
Fluocinolone Acetonide 0.025%

Otic solution

Sterile
Preservative-free

FOR USE IN THE EAR ONLY

Contents:
14 vials
0.25 mL each
(Deliverable volume)

WraSer, LLC

Salvat